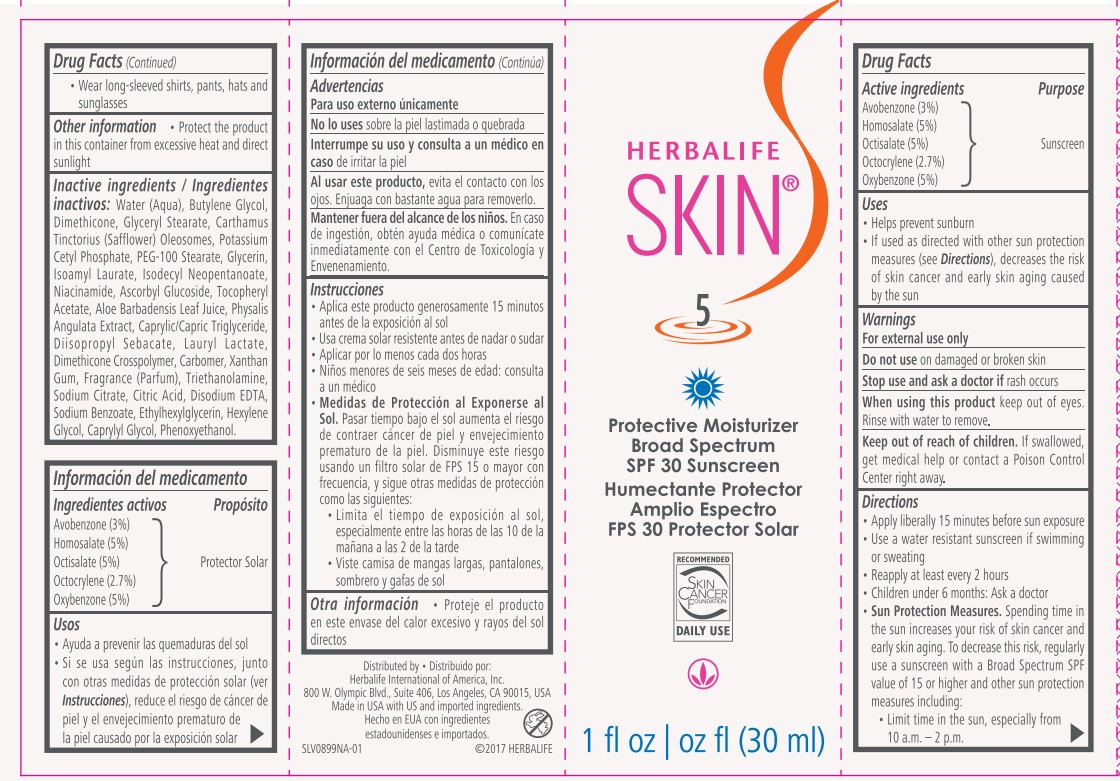 DRUG LABEL: Herbalife Skin Protective Moisturizer SPF 30
NDC: 51785-899 | Form: CREAM
Manufacturer: Herbalife International of America Inc.
Category: otc | Type: HUMAN OTC DRUG LABEL
Date: 20191218

ACTIVE INGREDIENTS: OCTOCRYLENE 0.8505 g/30 mL; AVOBENZONE 0.9711 g/30 mL; HOMOSALATE 1.56 g/30 mL; OCTISALATE 1.515 g/30 mL; OXYBENZONE 1.8 g/30 mL
INACTIVE INGREDIENTS: NIACINAMIDE; PHYSALIS ANGULATA; HEXYLENE GLYCOL; ALOE VERA LEAF; ISOAMYL LAURATE; DIISOPROPYL SEBACATE; PHENOXYETHANOL; ASCORBYL GLUCOSIDE; CARTHAMUS TINCTORIUS (SAFFLOWER) OLEOSOMES; SODIUM CITRATE; EDETATE DISODIUM; XANTHAN GUM; ANHYDROUS CITRIC ACID; POTASSIUM CETYL PHOSPHATE; PEG-100 STEARATE; GLYCERIN; ISODECYL NEOPENTANOATE; MEDIUM-CHAIN TRIGLYCERIDES; LAURYL LACTATE; .ALPHA.-TOCOPHEROL ACETATE; TROLAMINE; SODIUM BENZOATE; DIMETHICONE/DIENE DIMETHICONE CROSSPOLYMER; DIMETHICONE; WATER; CAPRYLYL GLYCOL; CARBOMER HOMOPOLYMER TYPE B (ALLYL SUCROSE CROSSLINKED); GLYCERYL MONOSTEARATE; BUTYLENE GLYCOL; ETHYLHEXYLGLYCERIN

Herbalife Skin Protective Moisturizer SPF 30

Drug Facts

Purpose

Sunscreen

Active ingredients

Avobenzone (3%)

Homosalate (5%)

Octisalate (5%)

Octocrylene (2.7%)

Oxybenzone (5%)

Uses

•Helps prevent sunburn

• If used as directed with other sun protection measures (see Directions), decreases the risk of skin cancer and early skin aging caused by the sun

Warnings

For external use only

Do not use on damaged or broken skin

Stop use and ask a doctor if rash occurs

When using this product keep out of eyes. Rinse with water to remove

Keep out of reach of children. If swallowed, get medical help or contact a Poison Control Center right away.

Directions

• Apply liberally 15 minutes before sun exposure

• Use a water resistant sunscreen if swimming or sweating

• Reapply at least every 2 hours

• Children under 6 months: Ask a doctor

• Sun Protection Measures. Spending time in the sun increases your risk of skin cancer and early skin aging. To decrease this risk, regularly use a sunscreen with a Broad Spectrum SPF value of 15 or higher and other sun protection measures including:

• Limit time in the sun, especially from 10 a.m. – 2 p.m.

• Wear long-sleeved shirts, pants, hats and sunglasses

Other information

• Protect the product in this container from excessive heat and direct sunlight

INACTIVE INGREDIENT

Inactive ingredients: Water (Aqua), Butylene Glycol, Dimethicone, Glyceryl Stearate, Carthamus Tinctorius (Safflower) Oleosomes, Potassium Cetyl Phosphate, PEG-100 Stearate, Glycerin, Isoamyl Laurate, Isodecyl Neopentanoate, Niacinamide, Ascorbyl Glucoside, Tocopheryl Acetate, Aloe Barbadensis Leaf Juice, Physalis Angulata Extract, Caprylic/Capric Triglyceride, Diisopropyl Sebacate, Lauryl Lactate, Dimethicone Crosspolymer, Carbomer, Xanthan Gum, Fragrance (Parfum), Triethanolamine, Sodium Citrate, Citric Acid, Disodium EDTA, Sodium Benzoate, Ethylhexylglycerin, Hexylene Glycol, Caprylyl Glycol, Phenoxyethanol.

Distributed by:

Herbalife International of America, Inc.

800 W. Olympic Blvd., Suite 406, Los Angeles, CA 90015, USA

Made in USA with US and imported ingredients.

©2017 HERBALIFE

PACKAGE LABEL

HERBALIFE

SKIN

5

Protective Moisturizer Broad Spectrum SPF 30 Sunscreen

1 fl oz (30 ml)